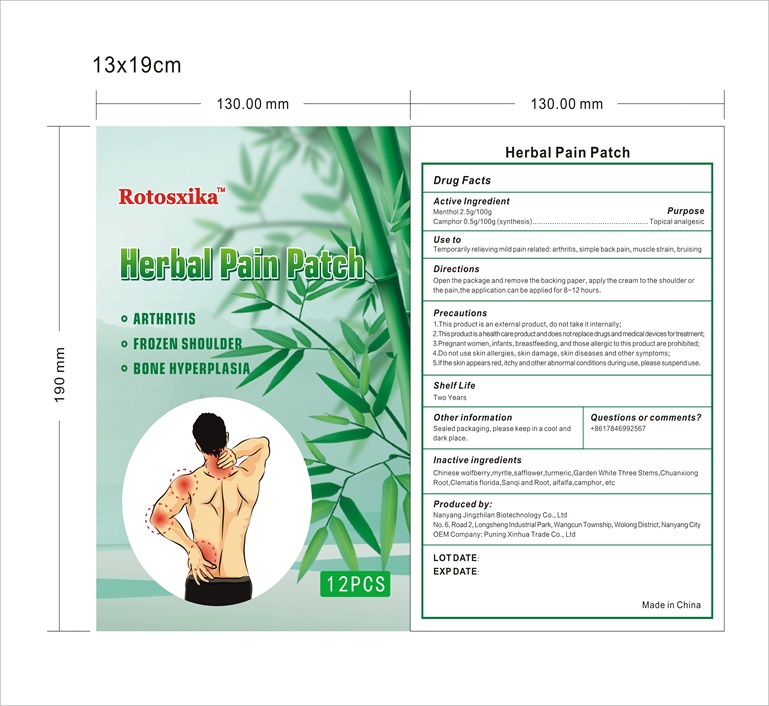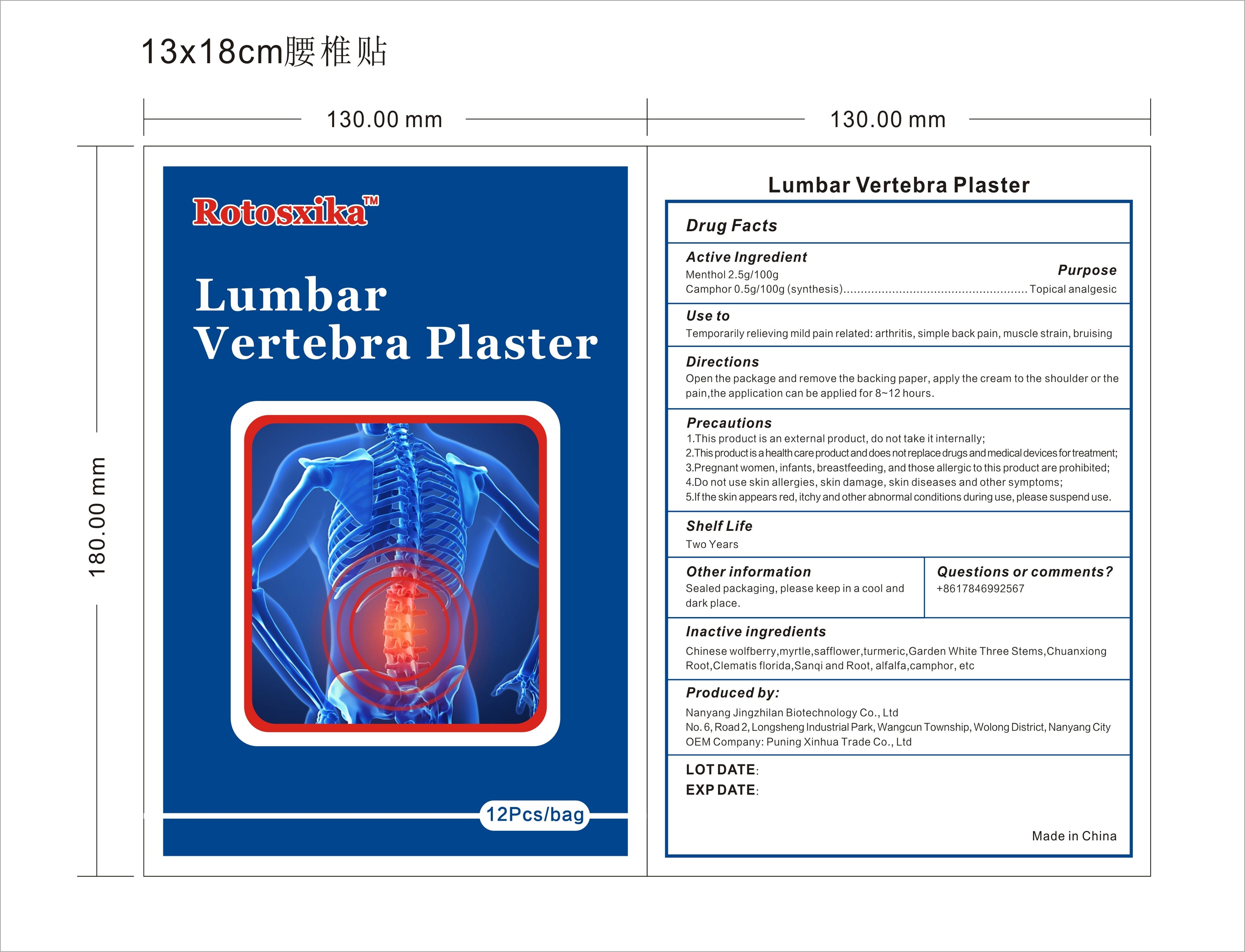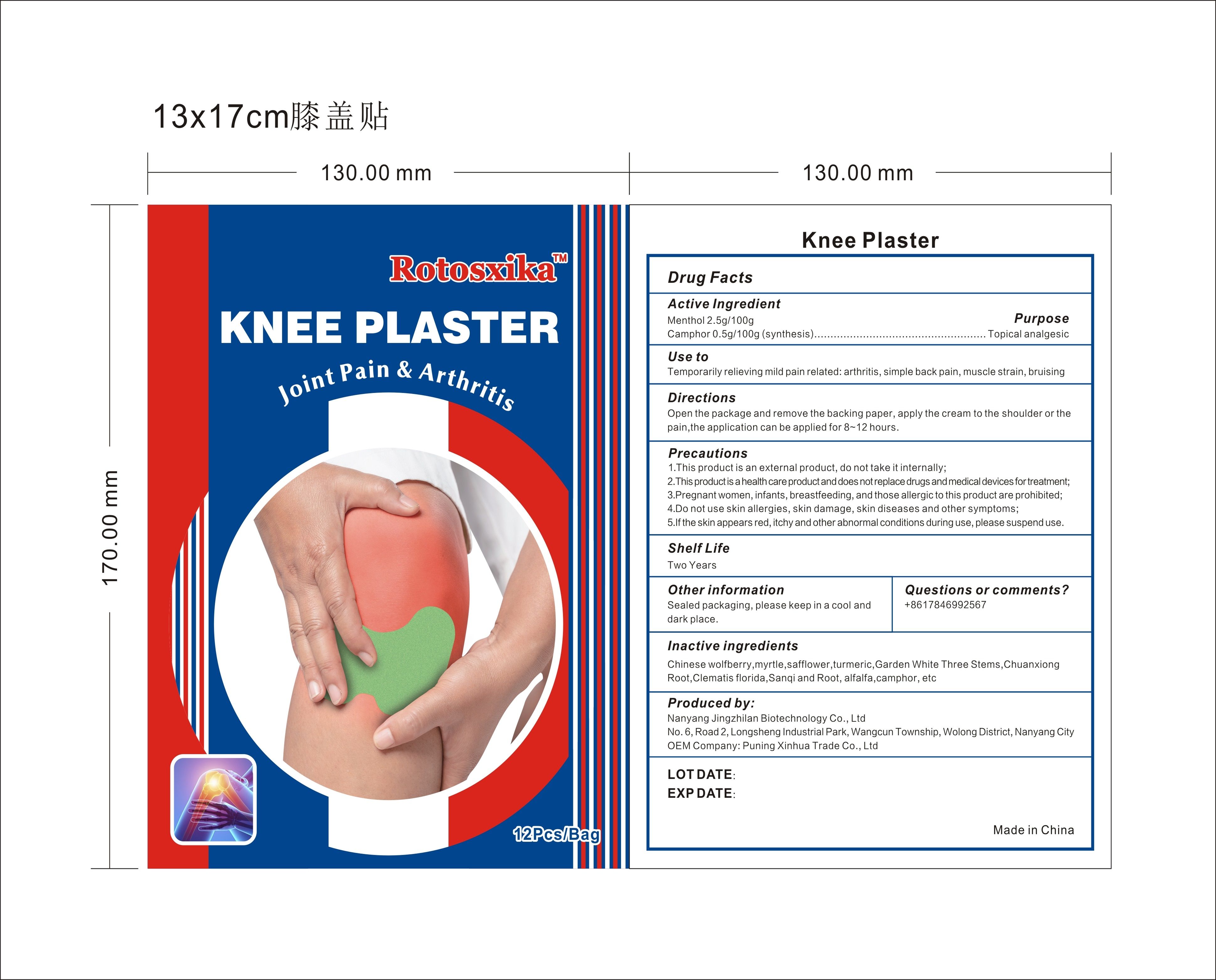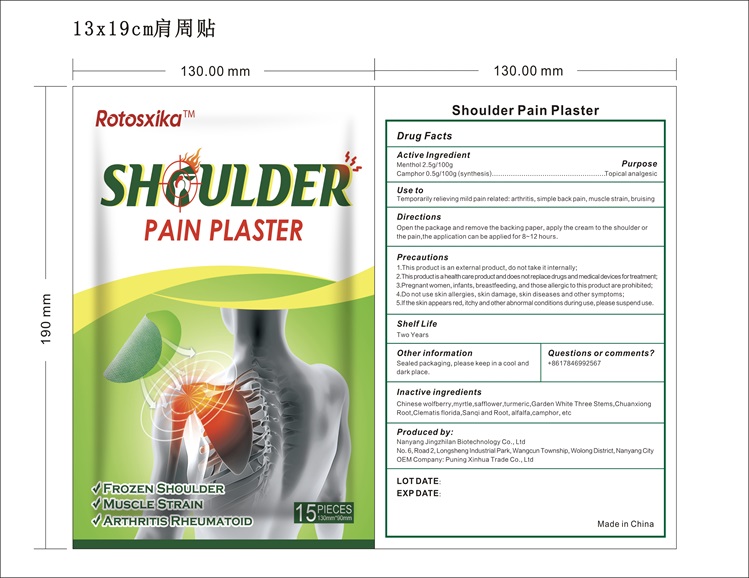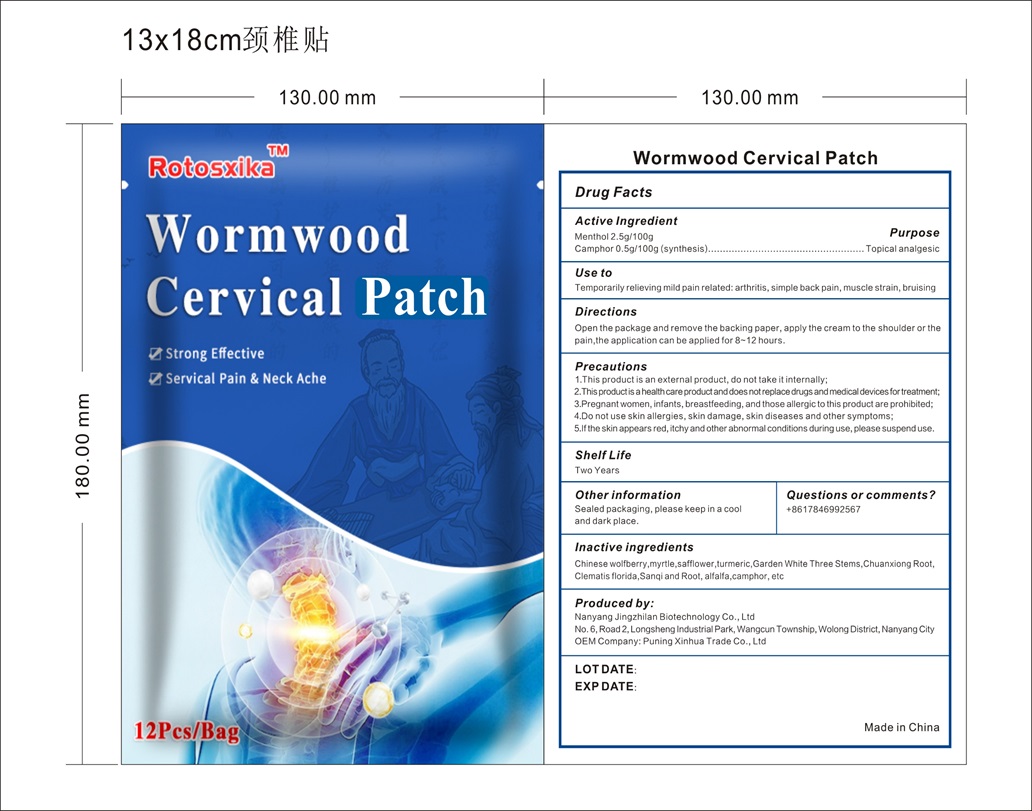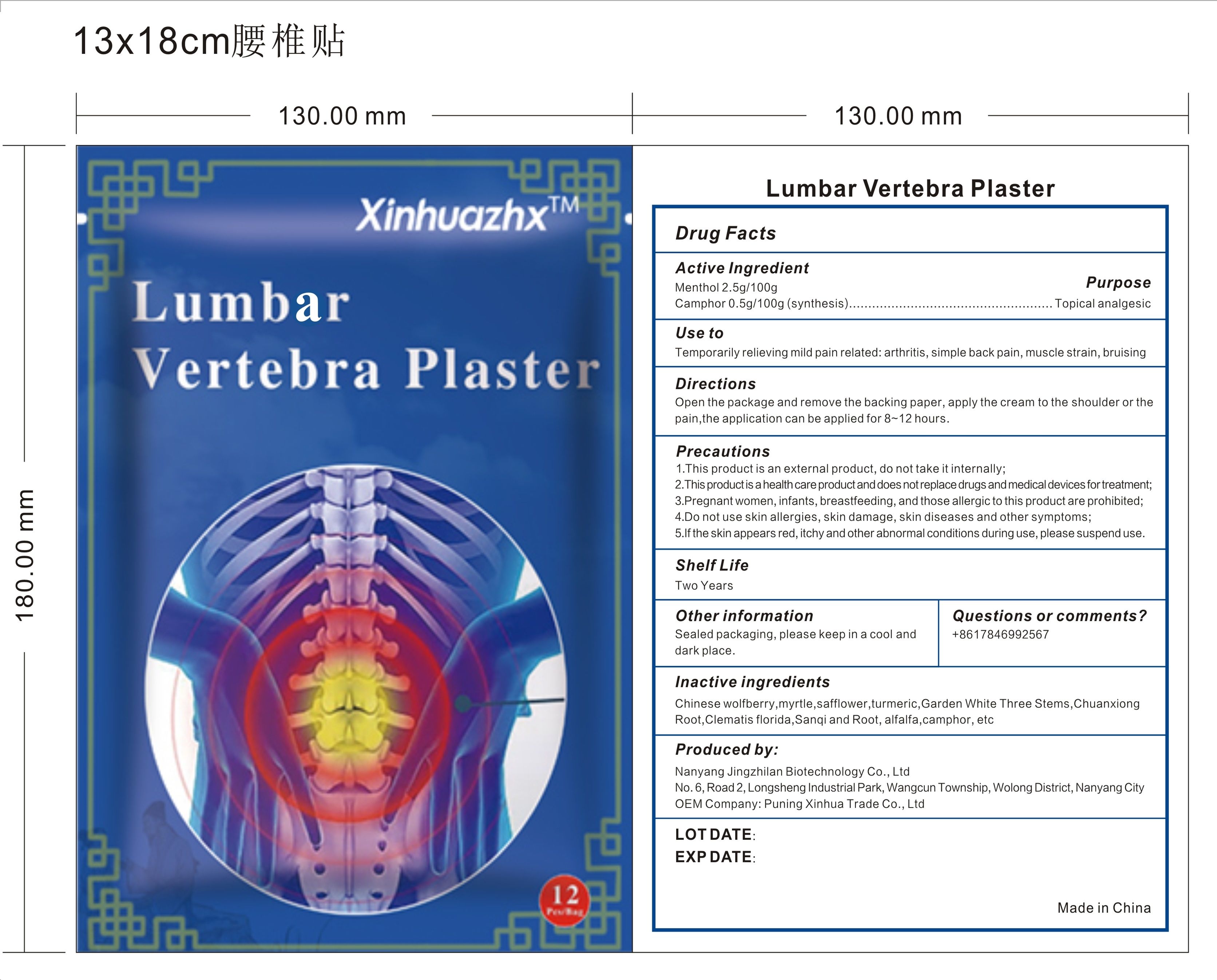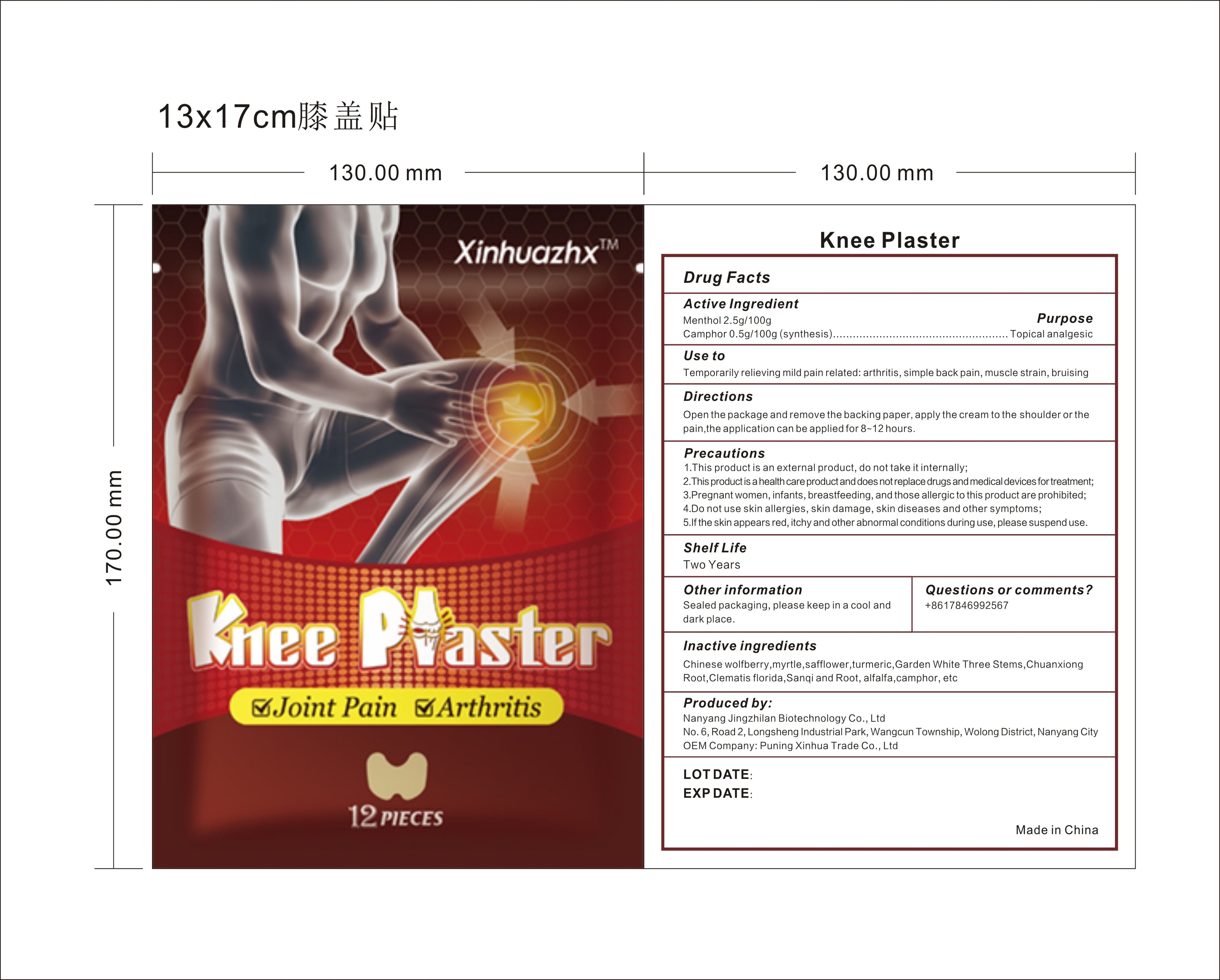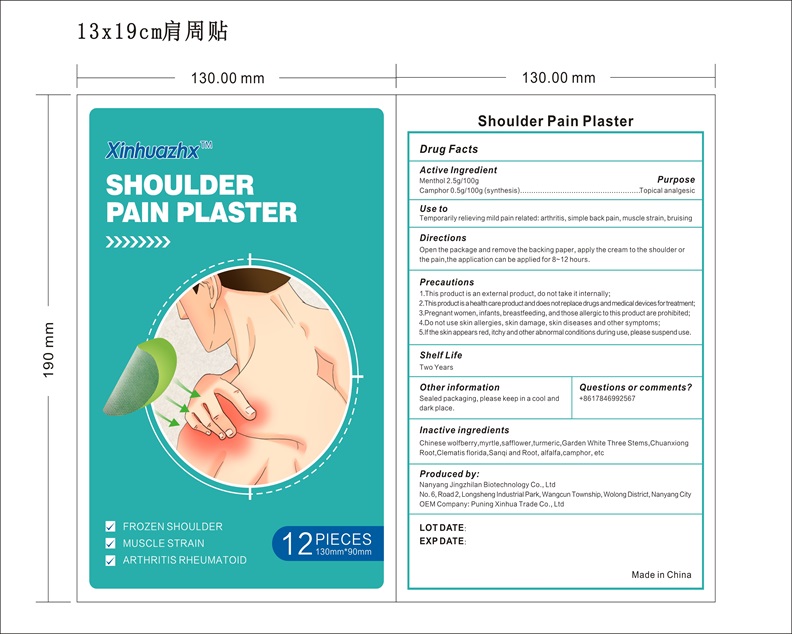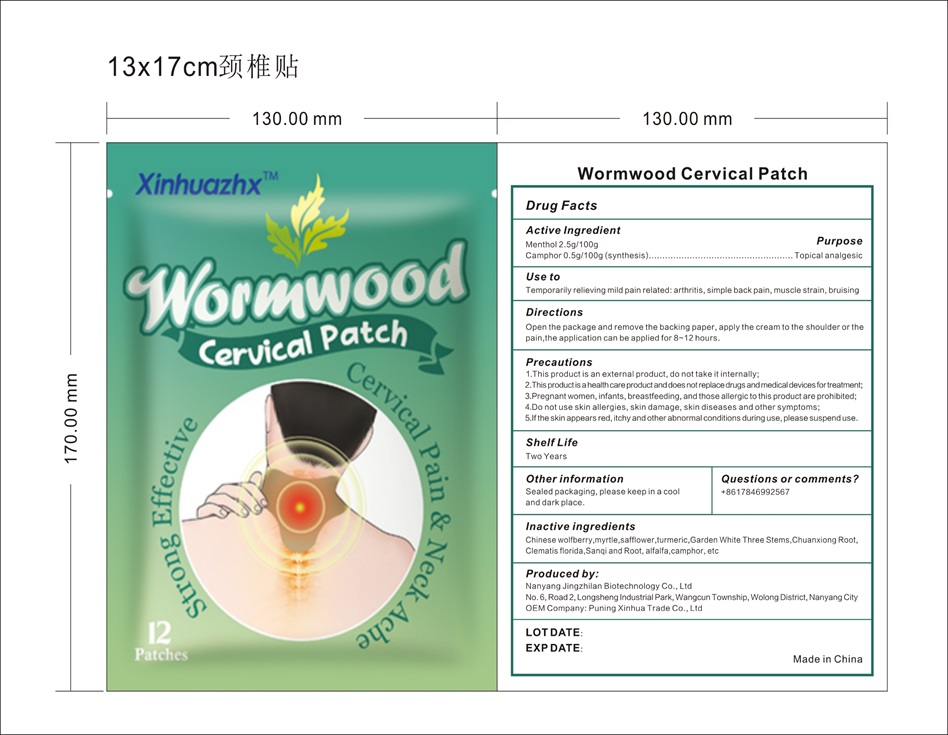 DRUG LABEL: Rotosxika Lumbat Vertebra Plaster
NDC: 83702-007 | Form: PATCH
Manufacturer: Puning Xinhua Trade Co., Ltd.
Category: otc | Type: HUMAN OTC DRUG LABEL
Date: 20230921

ACTIVE INGREDIENTS: CAMPHOR (SYNTHETIC) 0.5 g/100 g; MENTHOL 2.5 g/100 g
INACTIVE INGREDIENTS: MYRRH; SAFFLOWER

Active ingredient

Menthol 5g/100ml

Camphor 3g/100ml （synthesis）

Purpose: Topical analgesic

WARNINGS

Precautions:

1. This product is an external product, do not take it internally;

2. This product is a health care product and does notreplace drugs and medical devices for treatment;

3. Pregnant women, infants, breastfeeding, and those allergic to this product are prohibited;

4. Do not use skin allergies, skin damage, skin diseases and other symptoms;

5. If the skin appears red, itchy and other abnormal conditions during use, please suspend use.

DOSAGE AND ADMINISTRATION

Directions: Open the package and remove the backing paper, apply the cream to the shoulder or the pain, the application can be applied for 8-12 hours.

Shelf Life: Two Years

Other information: Sealed packaging, please keep in a cool and dark place.

Questions or comments? +8617846992567

INACTIVE INGREDIENT

Inactive ingredients: Chinese wolfberry, myrtle,safflower,turmeric, Garden White Three Stems, ChuanxiongRoot, Clematis florida, Sanqi and Root, alfalfa,camphor, etc

KEEP OUT OF REACH OF CHILDREN

Precautions: 3. Pregnant women, infants, breastfeeding, and those allergic to this product are prohibited;

STATEMENT OF IDENTITY

Produced by:
Nanyang Jingzhilan Biotechnology Co., Ltd
No. 6, Road 2, Longsheng Industrial Park, Wangcun Township, Wolong District, Nanyang City
OEM Company: Puning Xinhua Trade Co., Ltd

Made in China

INDICATIONS AND USAGE

Use to: Temporarily relieving mild pain related: arthritis, simple back pain, muscle strain, bruisinga

SEE LABEL